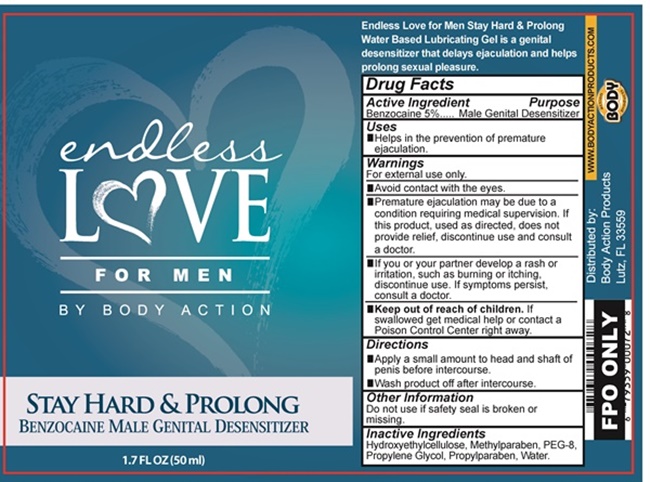 DRUG LABEL: endless Love
NDC: 70742-072 | Form: GEL
Manufacturer: Product Max Group Inc
Category: otc | Type: HUMAN OTC DRUG LABEL
Date: 20160807

ACTIVE INGREDIENTS: BENZOCAINE 2410 mg/50 mL
INACTIVE INGREDIENTS: HYDROXYETHYL CELLULOSE (140 MPA.S AT 5%); METHYLPARABEN; POLYETHYLENE GLYCOL 400; PROPYLENE GLYCOL; PROPYLPARABEN; WATER

Endless Love - 072

Drug Facts Active Ingredient

Benzocaine 5%

Purpose

Male Genital Desensitizer

Keep out of reach of children

If swallowed get medical help or contact a Poison Control Center right away.

Uses

Helps in the prevention of premature ejaculation.

Warnings

For external use only.

- Avoid contact with the eyes

- Premature ejaculation may be due to a condition requiring medical supervision. If this product, used as directed, does not provide relief, discontinue use and consult a doctor.

- If you or your partner develop a rash or irritation, such as burning or itching, discontinue use. If symptoms persist, consult a doctor.

Directions

- Apply a small amount to head and shaft of penis before intercourse.

- Wash product off after intercourse.

Other Information

Do not use if safety seal is broken or missing.

Inactive Ingredients

Hydroxyethylcellulose, Methylparaben, PEG-8, Propylene Glycol, Propylparaben, Water

endless LOVE FOR MEN product label

endless LOVE

FOR MEN

BY BODY ACTION

STAY HARD & PROLONG
BENZOCAINE MALE GENITAL DESENSITIZER

1.7 FL OX (50 ml)

Endless Love for Men Stay Hard & Prolong Water Based Lubricating Gel is a genital desensitizer that delays ejaculation and helps prolong sexual pleasure.

www.BODYACTIONPRODUCTS.COM

ACTION BODY PRODUCTS

Distributer by:
Body Action Products

Lutz, FL 33559